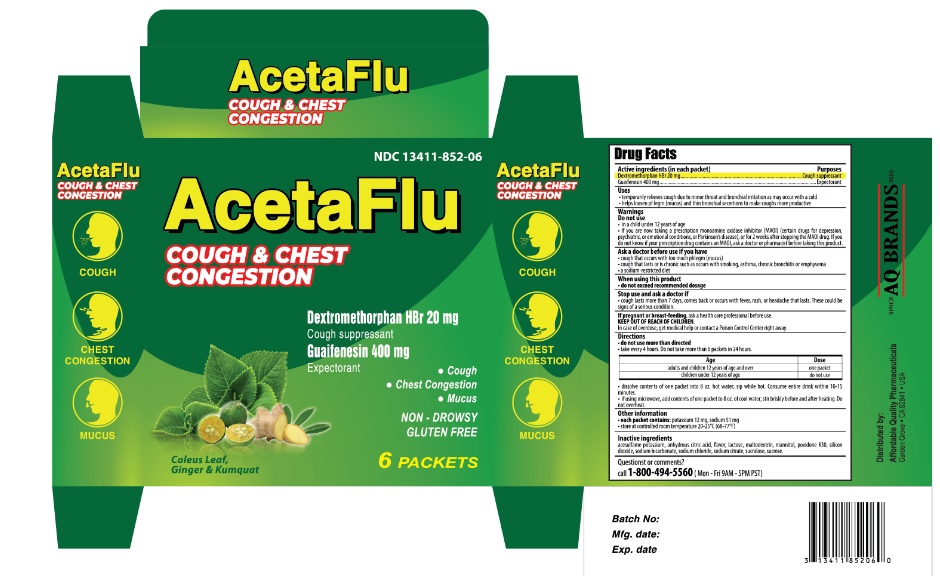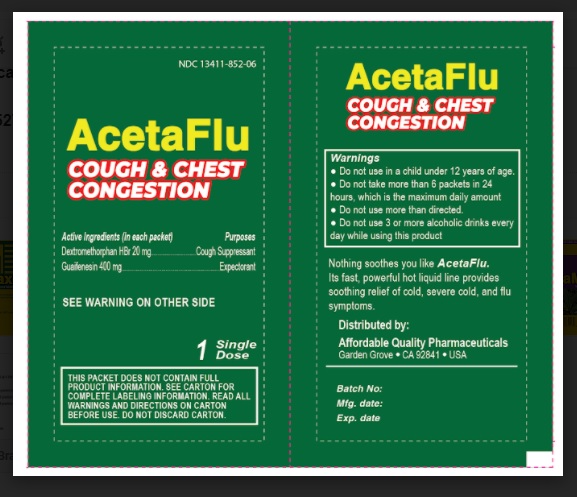 DRUG LABEL: ACETAFLU COUGH AND CHEST CONGESTION
NDC: 13411-852 | Form: POWDER
Manufacturer: Advanced Pharmaceutical Services, Inc. Dba Affordable Quality Pharmaceuticals
Category: otc | Type: HUMAN OTC DRUG LABEL
Date: 20200831

ACTIVE INGREDIENTS: DEXTROMETHORPHAN HYDROBROMIDE 20 mg/5 g; GUAIFENESIN 400 mg/5 g
INACTIVE INGREDIENTS: ACESULFAME POTASSIUM; ANHYDROUS CITRIC ACID; LACTOSE MONOHYDRATE; MALTODEXTRIN; MANNITOL; POVIDONE K30; SILICON DIOXIDE; SODIUM BICARBONATE; SODIUM CHLORIDE; SODIUM CITRATE; SUCRALOSE; SUCROSE

ACETAFLU COUGH & CHEST CONGESTION

Active Ingredients

Dextromethorphan HBr 20 mg

Guaifenesin 400 mg

Purposes

- Cough suppressant
- Expectorant

Uses

- temporarily relieves cough due to minor throat and bronchial irritation as may occur with a cold
- helps loosen phlegm (mucus) and thin bronchial secretions to make coughs more productive

Warnings

Do not use

- in a child under 12 years of age
- If you are now taking a prescription monoamine oxidase inhibitor (MAOI) (certain drugs for depression, psychiatric, or emotional conditions, or Parkinson’s disease), or for 2 weeks after stopping the MAOI drug. If you do not know if your prescription drug contains an MAOI, ask a doctor or pharmacist before taking this product.

Ask a doctor before use if you have

- cough that occurs with too much phlegm (mucus)
- cough that lasts or is chronic such as occurs with smoking, asthma, chronic bronchitis or emphysema
- a sodium-restricted diet

When using this product

- do not exceed recommended dosage

Stop use and ask a doctor if

- cough lasts more than 7 days, comes back or occurs with fever, rash, or headache that lasts. These could be signs of a serious condition.

If pregnant or breast-feeding,

- ask a health care professional before use.

Keep out of reach of children.

In case of overdose, get medical help or contact a Poison Control Center right away.

Directions

do not use more than directed
take every 4 hours. Do not take more than 6 packets in 24 hours.

Age | Dose
adults and children 12 years of age and over | one packet
children under 12 years of age | do not use

- dissolve contents of one packet into 8 oz. hot water; sip while hot. Consume entire drink within 10-15 minutes.
- if using microwave, add contents of one packet to 8 oz. of cool water; stir briskly before and after heating.
- Do not overheat.

Other information

- each packet contains: potassium 12 mg, sodium 51 mg.
- store at controlled room temperature 20-25°C (68-77°F).

Inactive Ingredients.

acesulfame potassium, anhydrous citric acid, flavor, lactose, maltodextrin, mannitol, povidone K30, silicon dioxide, sodium bicarbonate, sodium chloride, sodium citrate, sucralose, sucrose